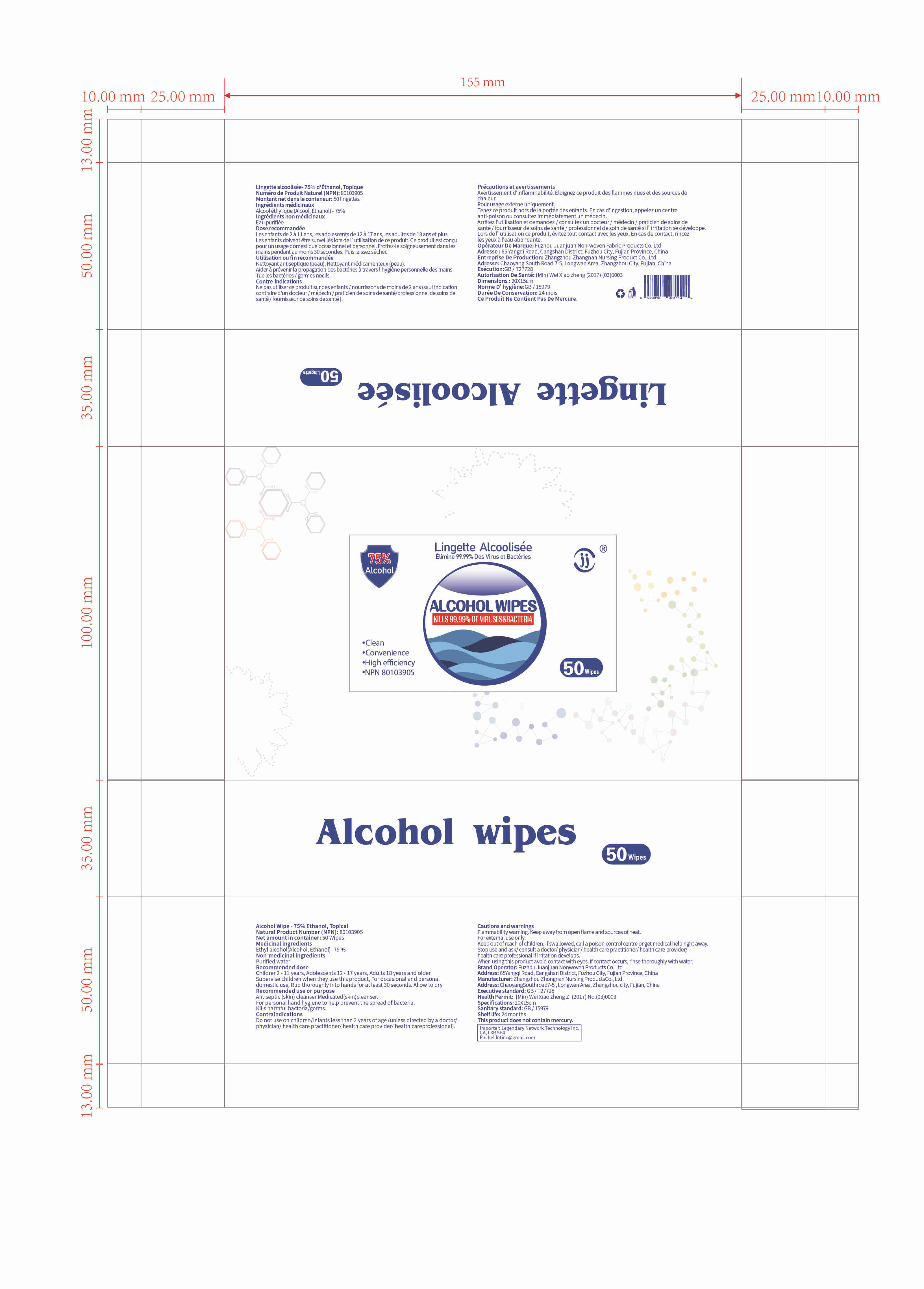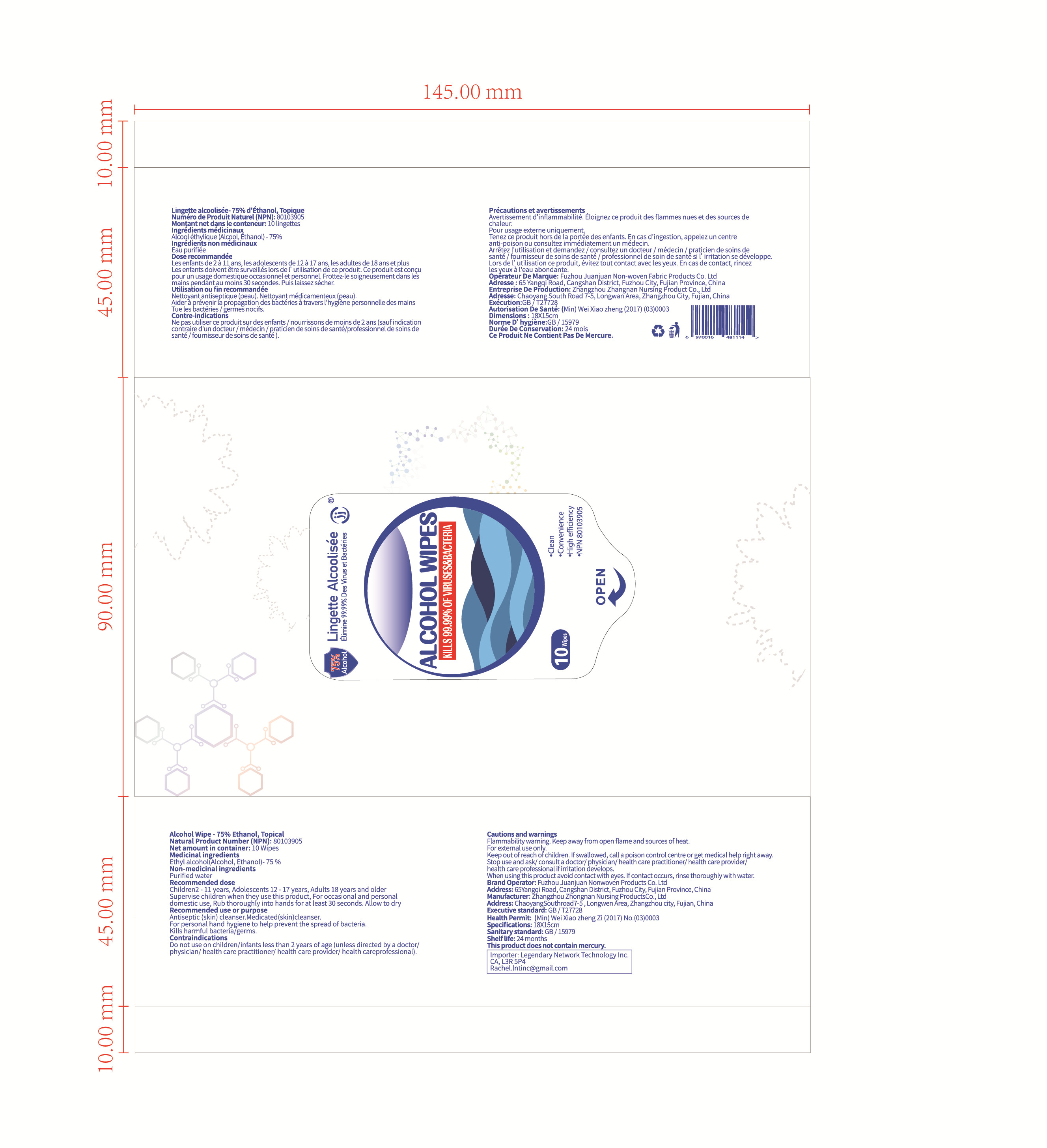 DRUG LABEL: Alcohol Wipes
NDC: 54141-001 | Form: CLOTH
Manufacturer: Fuzhou Juanjuan Non-Woven Products Co., Ltd.
Category: otc | Type: HUMAN OTC DRUG LABEL
Date: 20201213

ACTIVE INGREDIENTS: ALCOHOL 230 g/50 1
INACTIVE INGREDIENTS: WATER

DOSAGE AND ADMINISTRATION

Store in a cool and dry place.

INACTIVE INGREDIENT

Purified Water

Non-woven fabric

INDICATIONS AND USAGE

Rub thoroughly into hands for at least 30 seconds.Allow to dry

ACTIVE INGREDIENT

Ethyl Alcohol

Keep out of reach of children. If swallowed, call a poison control centre or get medical help right away.

PURPOSE

Disinfection
Sterilization
No Rinseing

WARNINGS

Flammability warning.Keep away from open flame and sources of heat.For externaluse only.